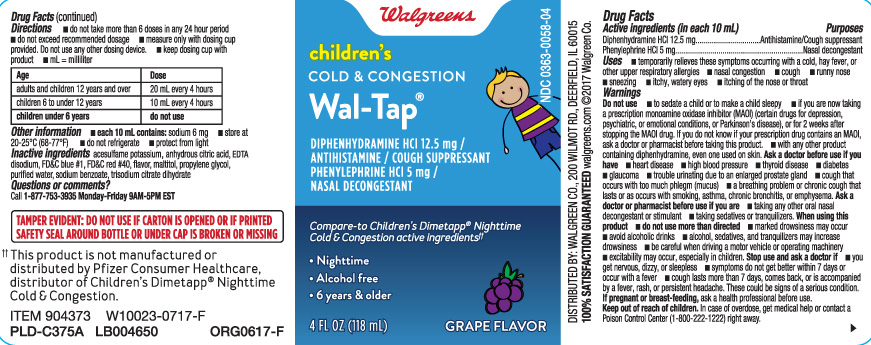 DRUG LABEL: Cold and Congestion
NDC: 0363-0058 | Form: LIQUID
Manufacturer: Walgreens
Category: otc | Type: HUMAN OTC DRUG LABEL
Date: 20231009

ACTIVE INGREDIENTS: DIPHENHYDRAMINE HYDROCHLORIDE 12.5 mg/10 mL; PHENYLEPHRINE HYDROCHLORIDE 5 mg/10 mL
INACTIVE INGREDIENTS: FD&C BLUE NO. 1; FD&C RED NO. 40; PROPYLENE GLYCOL; WATER; SODIUM BENZOATE; TRISODIUM CITRATE DIHYDRATE; ANHYDROUS CITRIC ACID; ACESULFAME POTASSIUM; MALTITOL; EDETATE DISODIUM

Drug Facts

Active ingredients (in each 10 mL)

Diphenhydramine HCI 12.5 mg

Phenylephrine HCI 5 mg

Purposes

Antihistamine/Cough suppressant

Nasal decongestant

Uses

- temporarily relieves these symptoms occuring with a cold, hay fever, or other upper respiratory allergies
  - nasal congestion
  - cough
  - runny nose
  - sneezing
  - itchy, watery eyes
  - itching of the nose or throat

Warnings

Do not use

- to sedate a child or to make a child sleepy
- if you are now taking a prescription monoamine oxidase inhibitor (MAOI) (certain drugs for depression, psychiatric or emotional conditions, or Parkinson's disease), or for 2 weeks after stopping the MAOI drug. If you do not know if your prescription drug contains an MAOI, ask a doctor or pharmacist before taking this product.
- with any other product containing diphenhydramine, even one used on skin.

Ask a doctor before use if you have

- heart disease
- high blood pressure
- thyroid disease
- diabetes
- glaucoma
- trouble urinating due to an enlarged prostate gland
- cough that occurs with too much phlem (mucus)
- a breathing problem or chronic cough that last or as occurs with smoking, asthma, chronic bronchitis, or emphysena.

Ask a doctor or pharmacist before use if you are

- taking any other oral nasal decongestant or stimulant
- taking sedatives or tranquilizers

When using this product

- do not use more than directed
- marked drowsiness may occur
- avoid alcoholic drinks
- alcohol, sedatives, and tranquilizers may increase drowsiness
- be careful when driving a motor vehicle or operating machinery
- excitability may occur, especially in children

Stop use and ask a doctor if

- you get nervous, dizzy or sleepless
- symptoms do not get better within 7 days or occur with a fever
- cough lasts more than 7 days, comes back, or is accompanied by a fever, rash, or persistent headache.

These could be signs of a serious condition.

If pregnant or breast-feeding,

ask a health professional before use.

Keep out of reach of children.

In case of overdose, get medical help or contact a Poison Control Center (1-800-222-1222) right away.

Directions

- do not take more than 6 doses in any 24-hour period
- do not exceed recommended dosage
- measure only with dosing cup provided. Do not use any other dosing device.
- keep dosing cup with product
- mL = milliliter

age | dose
adults and children 12 years and over | 20 mL every 4 hours
children 6 to 11 years | 10 mL every 4 hours
children under 6 years | do not use

Other information

- each 10 mL contains: sodium 6mg
- store at 20-25°C (68-77°F)
- Do not refrigerate
- protect from light

Inactive ingredients

acesulfame potassium anhydrous citric acid, EDTA disodium, FD&C blue #1, FD&C red # 40, flavor, maltitol, propylene glycol, purified water, sodium benzoate, trisodium citrate dihydrate

Questions or comments?

Call 1-877-753-3935 Monday-Friday 9AM-5PM EST

Principal Display Panel

children's

COLD & CONGESTION

DIPHENHYDRAMINE HCI 12.5 mg / ANTIHISTAMINE / COUGH SUPPRESSANT

PHENYLEPHRINE HCI 5 mg / NASAL DECONGESTANT

Compare-to Children's Dimetapp® Nighttime Cold & Congestion active ingredients††

- Nighttime
- Alcohol Free
- 6 years & older

FL OZ (mL)

GRAPE FLAVOR

TAMPER EVIDENT: DO NOT USE IF CARTON IS OPENED OR IF PRINTED SAFETY SEAL AROUND BOTTLE OR UNDER CAP IS BROKEN OR MISSING.

DISTRIBUTED BY : WALGREEN CO

200 WILMOT RD., DEERFIELD, IL 60015

walgreens.com

Package Label

WALGREENS Children's Cold & Congestion Grape Flavor